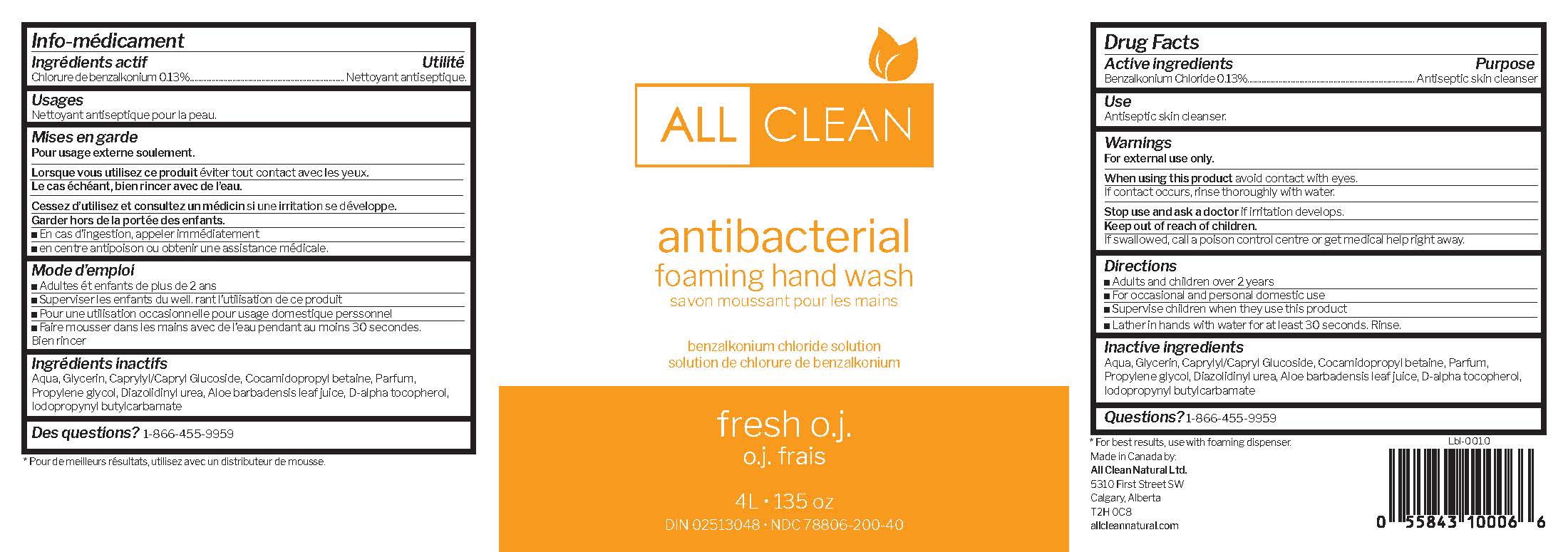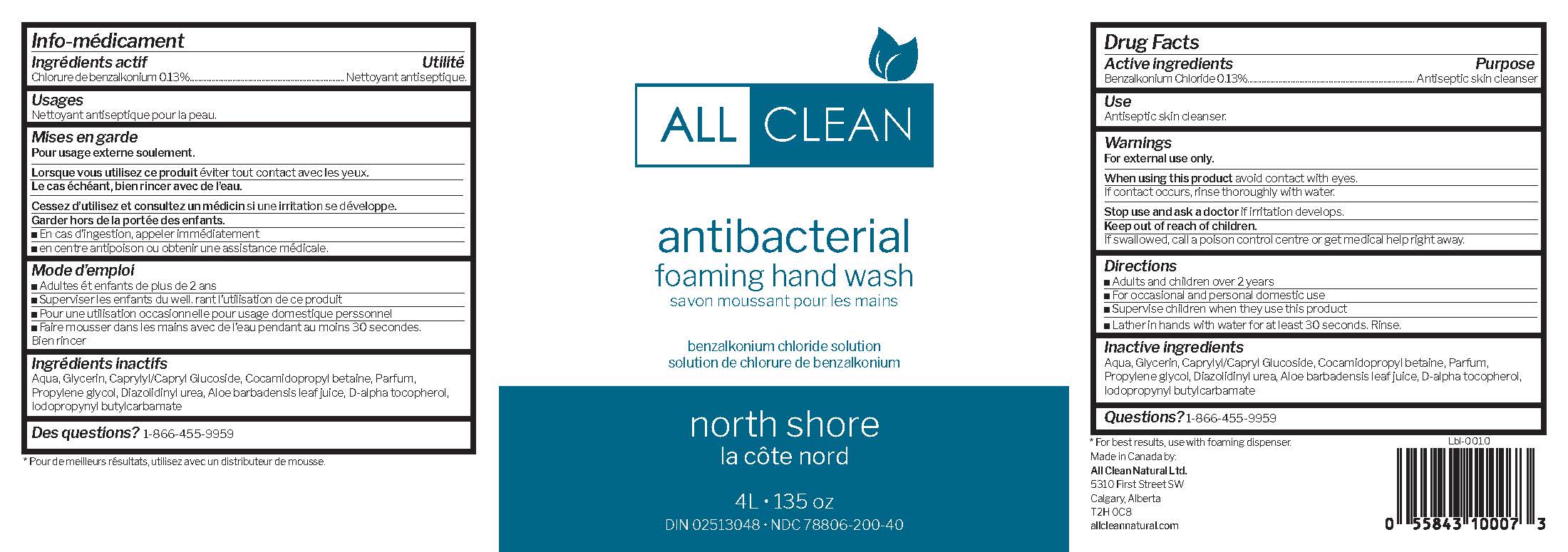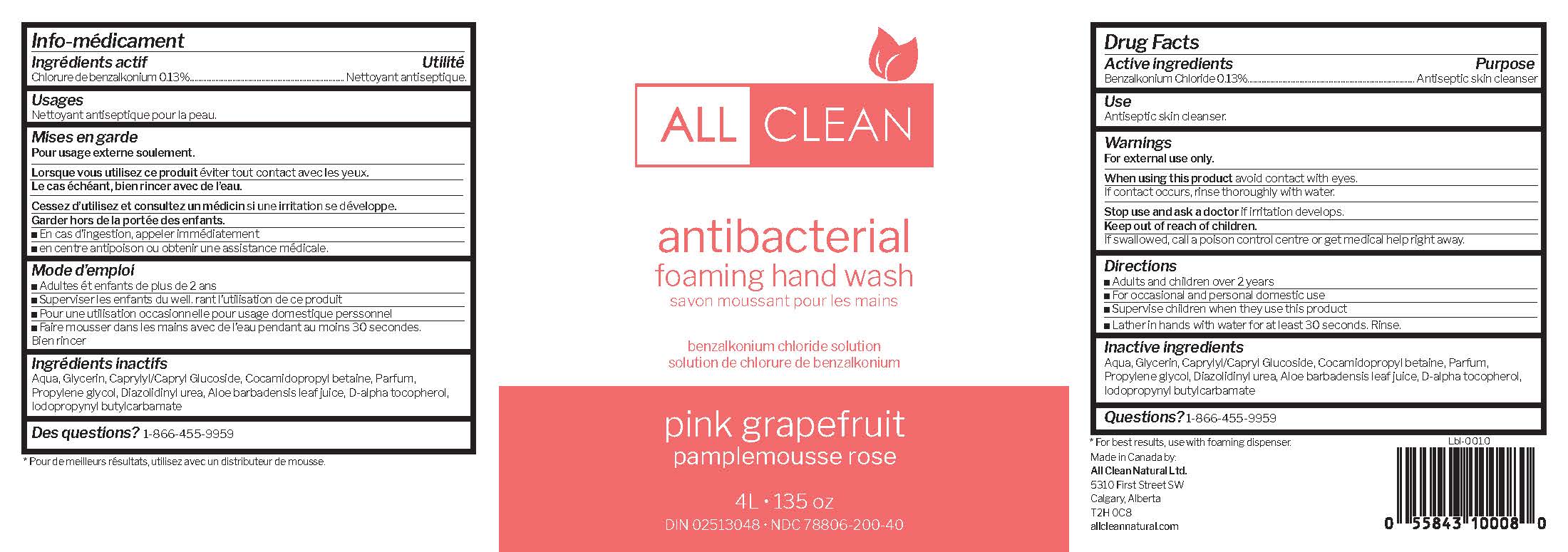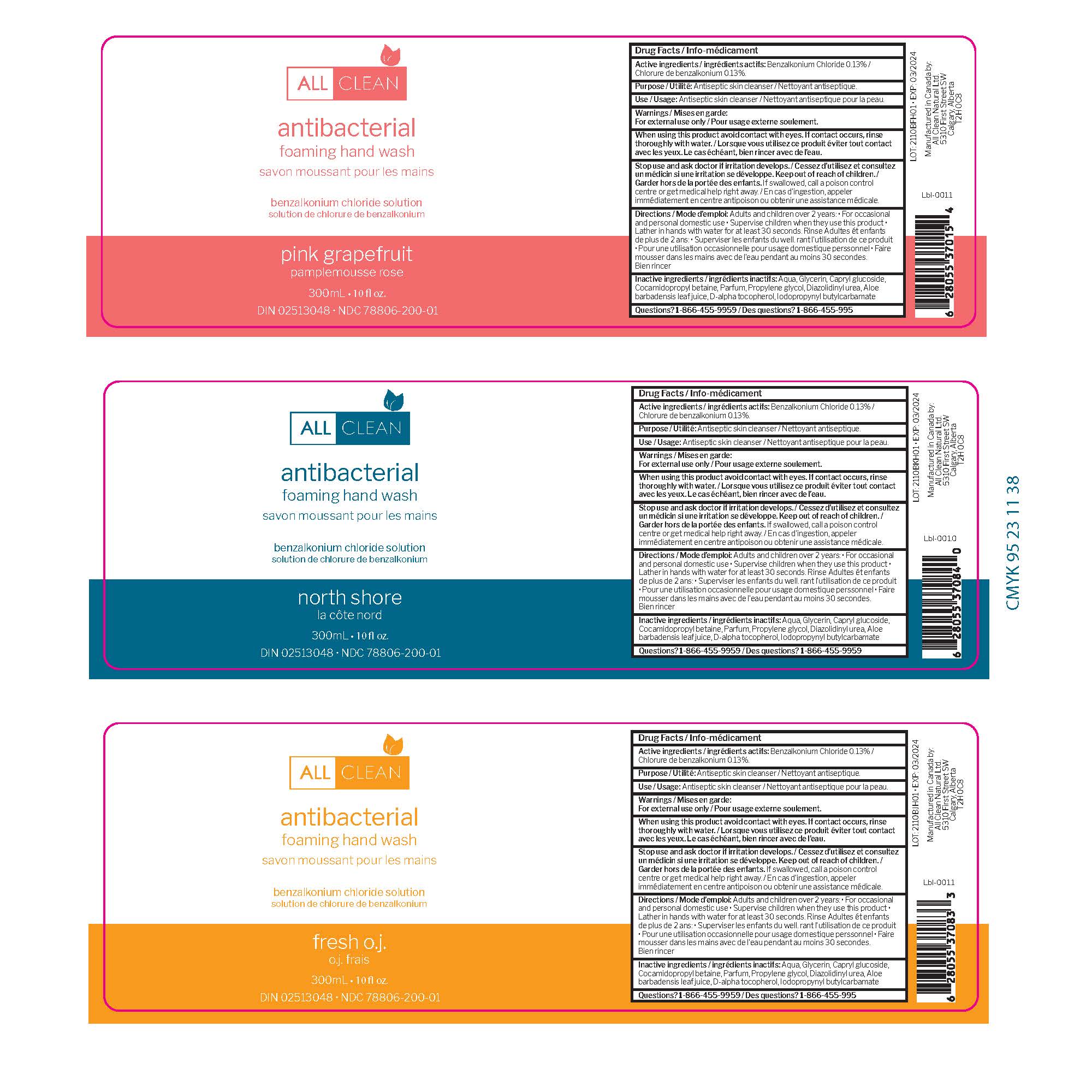 DRUG LABEL: All Clean Natural Antibacterial Foaming Hand Wash
NDC: 78806-200 | Form: SOAP
Manufacturer: All Clean Natural Ltd.
Category: otc | Type: HUMAN OTC DRUG LABEL
Date: 20210427

ACTIVE INGREDIENTS: BENZALKONIUM CHLORIDE 0.013 mg/1 mL
INACTIVE INGREDIENTS: PROPYLENE GLYCOL; CAPRYLYL GLUCOSIDE 0.1 mL/1 mL; GLYCERIN 0.03 mL/1 mL; WATER 0.7017 mL/1 mL; .ALPHA.-TOCOPHEROL ACETATE, D- 0.01 mL/1 mL; DIAZOLIDINYL UREA 0.05 mL/1 mL; ALOE 0.01 mL/1 mL

All Clean Natural Antibacterial Foaming Hand Wash

Active ingredients/ ingrédients actifs

Benzalkonium Chloride 0.13%/ Chlorure de benzalkonium 0.13%

PURPOSE

Antiseptic skin cleanser/ Nettoyant antiseptique

Use / Usage

Antiseptic skin cleanser/ Nettoyant antiseptique pour la peau

WARNING/ MISES EN GARDE

WHEN USING

When using this product avoid contact with eyes. If contact occurs, rinse thoroughly with water/ Lorsque vous utilisez ce produit éviter tout contact avec les yeux. Le cas échéant, bien rincer avec de l'eau.

STOP USE

Stop use and ask a doctor if irritation develops / Cessez d'utiliser et consultez un médecin si une irritation se développe

Keep out of reach of children. / Garder hors de la portée des enfants.

IF SWALLOWED

If swallowed, call a poison control centre or get medical help right away. / En cas d'ingestion, appeler immédiatement un centre antipoison ou obtenir une assistance médicale

Directions / Mode d'emploi

Adults and children over 2 years: • For occasional
and personal domestic use • Supervise children when they use this product •
Lather in hands with water for at least 30 seconds. Rinse Adultes ét enfants
de plus de 2 ans: • Superviser les enfants du well. rant l'utilisation de ce produit
• Pour une utilisation occasionnelle pour usage domestique perssonnel • Faire
mousser dans les mains avec de l'eau pendant au moins 30 secondes.
Bien rincer

Inactive ingredients/ ingrédients inactifs

Aqua, Glycerin, Capryl glucoside,
Cocamidopropyl betaine, Parfum, Propylene glycol, Diazolidinyl urea, Aloe
barbadensis leaf juice, D-alpha tocopherol, Iodopropynyl butylcarbamate